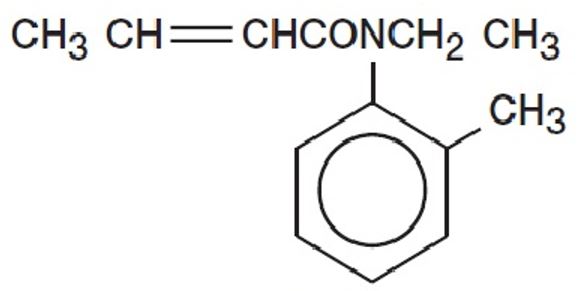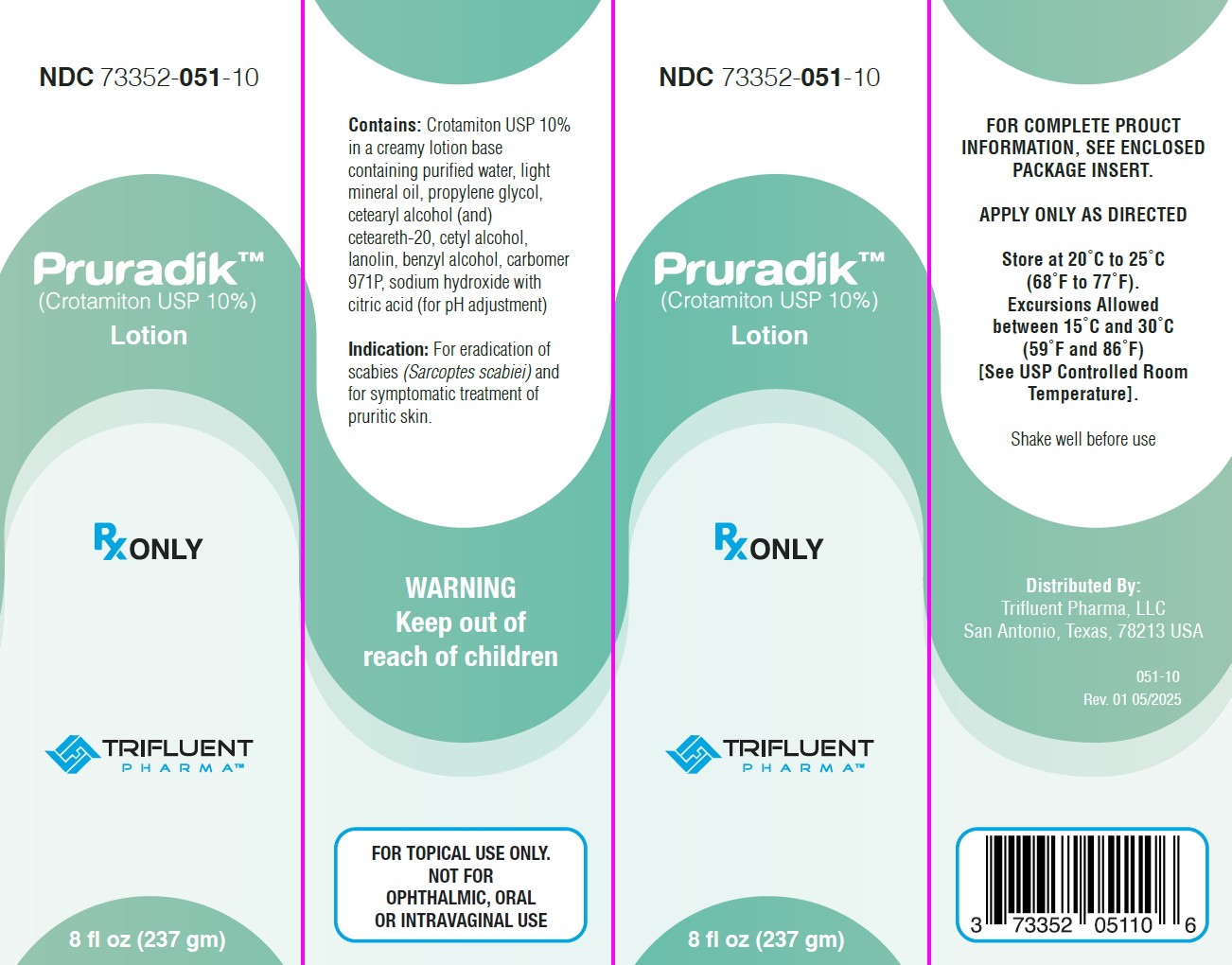 DRUG LABEL: Pruradik
NDC: 73352-051 | Form: LOTION
Manufacturer: Trifluent Pharma, LLC
Category: prescription | Type: HUMAN PRESCRIPTION DRUG LABEL
Date: 20250602

ACTIVE INGREDIENTS: CROTAMITON 100 mg/1 g
INACTIVE INGREDIENTS: WATER; MINERAL OIL; PROPYLENE GLYCOL; CETOSTEARYL ALCOHOL; POLYOXYL 20 CETOSTEARYL ETHER; CETYL ALCOHOL; LANOLIN; BENZYL ALCOHOL; CARBOMER HOMOPOLYMER TYPE A; SODIUM HYDROXIDE; CITRIC ACID MONOHYDRATE

PRURADIK™LOTION

WARNINGS AND PRECAUTIONS

FOR TOPICAL USE ONLY. NOT FOR OPHTHALMIC, ORAL OR INTRAVAGINAL USE.

Rx ONLY

INDICATIONS AND USAGE

Pruradik™ (crotamiton USP 10%) is a scabicidal and antipruritic agent as a lotion for topical use only. Crotamiton is a colorless to slightly yellowish oil, having a faint amine-like odor. It is miscible with alcohol and with methanol. Crotamiton is a mixture of the cis and trans isomers. Its molecular weight is 203. 28. Crotamiton is N-ethyl-N(o-methyl-phenyl) 2-butenamide and its structural formula is:

Pruradik lotion contains crotamiton USP 10% (100mg/ml) in a creamy lotion base containing purified water, light mineral oil, propylene glycol, cetearyl alcohol (and) cetearth-20, cetyl alcohol, lanolin, benzyl alcohol, carbomer 971P, sodium hydroxide with citric acid (for pH adjustment).

CLINICAL PHARMACOLOGY

CLINICAL PHARMACOLOGY: Pruradik™ lotion has scabicial and antipruritic actions. The mechanisms of these actions are not known. The pharmacokinetics of crotamiton and its degree of systemic absorption following topical application have not been determined.

GERIATRIC USE

Geriatric Use: Clinical studies with Pruradik (crotamiton USP) lotion did not include sufficient numbers of subjects aged 65 years and older to determine whether they respond differently than younger subjects. Other reported clinical experience has not identified differences in responses between elderly and younger patients, but greater sensitivity of some older individuals cannot be ruled out.

ADVERSE REACTIONS

ADVERSE REACTIONS: Primary irritation reactions such as dermatitis, pruritus and rash, and allergic sensitivity reactions have been reported in a few patients.

To report SUSPECTED ADVERSE REACTIONS, contact Trifluent Pharma, LLC at 1-888-927-5191 or FDA at 1-800-FDA-1088 or www.fda.gov/medwatch.

OVERDOSAGE

OVERDOSAGE: There is no specific informaton on the effect of overtreatment with repeated topical applications in humans. A death was reported but cause was not confirmed. Accidental oral ingestion may be accompanied by burning sensation in the mouth, irritation of the buccal, esophageal and gastric mucosa, nausea, vomiting, abdominal pain.

If accidental ingestion occurs, call your Poison Control Center.

DOSAGE AND ADMINISTRATION:

SHAKE WELL BEFORE USE.

In Scabies: Thoroughly massage into the skin of the whole body, from the chin down, paying particular attention to all folds and creases. A second application is advisable 24 hours later. Clothing and bed linen should be changed the next morning. A cleansing bath should be taken 48 hours after the last application.

In Pruritis: Massage gently into affected areas until medication is completely absorbed. Repeat as needed.

DIRECTIONS FOR PATIENTS WITH SCABIES:

1. Take a routine bath or shower. Thoroughly massage Pruradik™ lotion into the skin from the chin to the toes including folds and creases.

2. Put Pruradik lotion under fingernails after trimming the fingernails short, because scabies are likely to remain there. A toothbrush can be used to apply the Pruradik lotion under the fingernails. Immediately after use, the toothbrush should be wrapped in paper and thrown away. Use of the brush in the mouth could lead to poisoning.

3. A second application is advisable 24 hours leater.

4. Clothing and bed linen should be changed the next day. Contaminated clothing and bed linen may be dry-cleaned or washed in the hot cycle of the washing machine.

5. A cleansing bath should be taken 48 hours after the last application.

INDICATIONS AND USAGE: For eradication of scabies (Sarcoptes scabiei) and for symptomatic treatment of pruritic skin.

CONTRAINDICATIONS

CONTRAINDICATIONS: Pruradik lotion should not be applied topically to patients who develop a sensitivity or are allergic to it or who manifest a primary irritation response to topical medications.

WARNINGS

WARNINGS: If severe irritation or sensitization develops, treatment with this product should be discontinued and appropriate therapy instituted.

PRECAUTIONS

PRECAUTIONS: General: Pruradik lotion should not be applied in the eyes or mouth because it may cause irritation. It should not be applied to acutely inflamed skin or raw or weeping surfaces until acute inflammation has subsided.

PATIENT COUNSELING INFORMATION

Information for Patients: See "DIRECTIONS FOR PATIENTS WITH SCABIES."

Drug Interactions: None known.

CARCINOGENESIS AND MUTAGENESIS AND IMPAIRMENT OF FERTILITY

Carcinogenesis, Mutangenesis, Impairment of Fertility: Long-term carcinogenicity studies in animals have not been conducted.

PREGNANCY

Pregnancy (Category C): Animal reproduction studies have not been conducted with Pruradik (crotamiton USP) lotion. It is also not known whether Pruradik can cause fetal harm when applied to a pregnant woman or can affect reproduction capacity. Pruradik should be given to a pregnant woman only if clearly needed.

PEDIATRIC USE

Pediatric Use: Safety and effectiveness in children have not been established.

HOW SUPPLIED

HOW SUPPLIED: Pruradik (crotamitan USP) lotion, 10% is available in:

237 gm (NDC: 73352-051-10)

Rx ONLY

Mfd For:

Trifluent Pharma, LLC

San Antonio TX 78213

Rev 01 May 2025

KEEP OUT OF REACH OF CHILDREN.

STORAGE AND HANDLING

STORAGE: Store 20° to 25ºC (68°- 77°F). Excursions allowed between 15°and 30°C (59° and 86°F) [See USP Controlled Room Temperature].